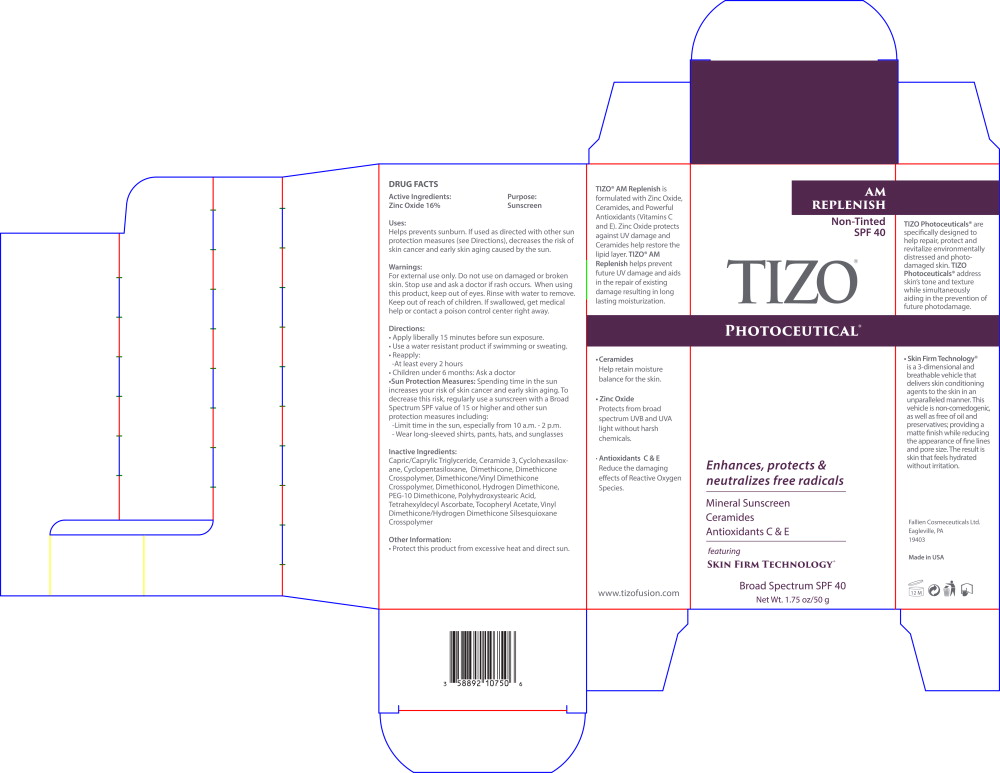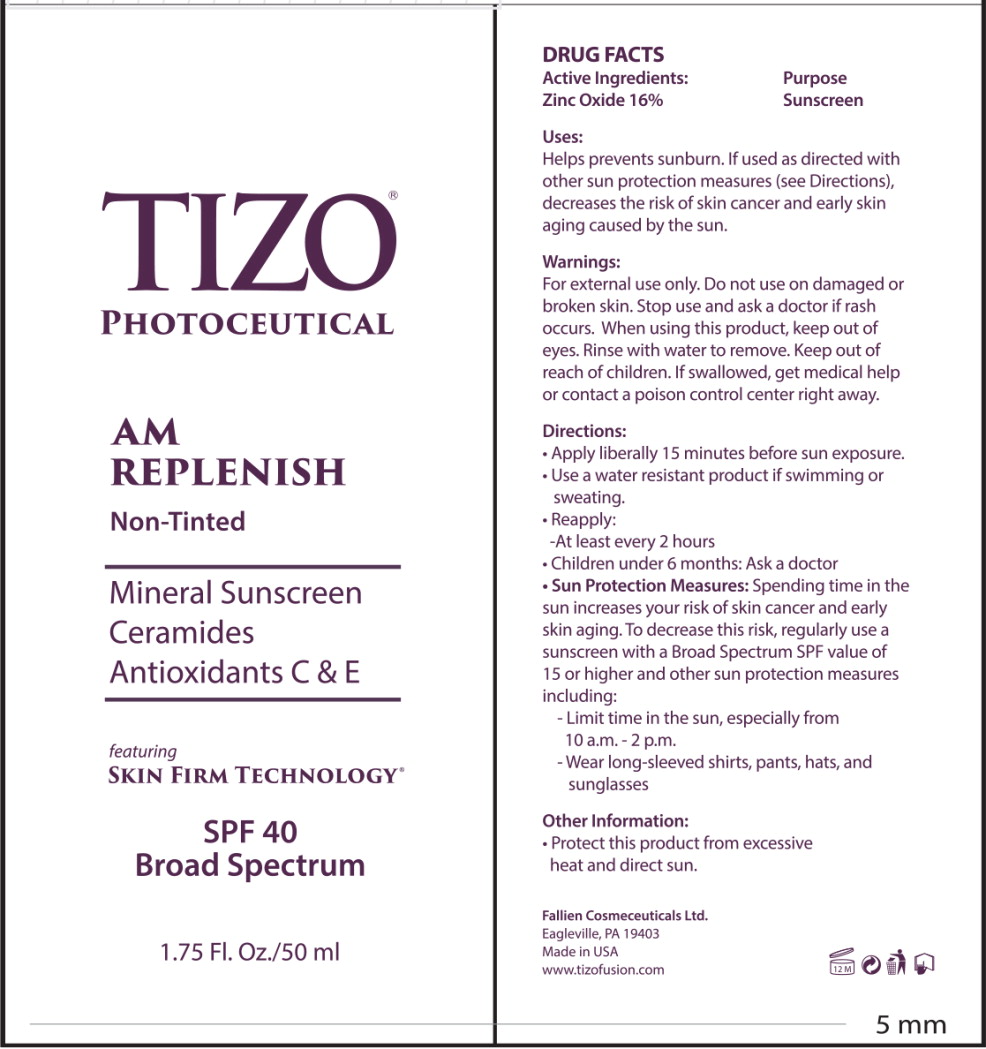 DRUG LABEL: TiZO Photoceutical AM Replenish Non-Tinted
NDC: 58892-107 | Form: CREAM
Manufacturer: Fallien Cosmeceuticals, LTD
Category: otc | Type: HUMAN OTC DRUG LABEL
Date: 20241114

ACTIVE INGREDIENTS: ZINC OXIDE 160 mg/1 g
INACTIVE INGREDIENTS: MEDIUM-CHAIN TRIGLYCERIDES; CERAMIDE NP; CYCLOMETHICONE 6; CYCLOMETHICONE 5; DIMETHICONE 20; DIMETHICONE CROSSPOLYMER (450000 MPA.S AT 12% IN CYCLOPENTASILOXANE); DIMETHICONE/VINYL DIMETHICONE CROSSPOLYMER (SOFT PARTICLE); DIMETHICONOL (2000 CST); HYDROGEN DIMETHICONE (20 CST); PEG-10 DIMETHICONE (600 CST); POLYHYDROXYSTEARIC ACID (2300 MW); TETRAHEXYLDECYL ASCORBATE; .ALPHA.-TOCOPHEROL ACETATE; VINYL DIMETHICONE/METHICONE SILSESQUIOXANE CROSSPOLYMER

DRUG FACTS

Active Ingredients:

Zinc Oxide 16%

Purpose:

Sunscreen

Uses:

Helps prevents sunburn. If used as directed with other sun protection measures (see Directions), decreases the risk of skin cancer and early skin aging caused by the sun.

Warnings:

For external use only. Do not use on damaged or broken skin. Stop use and ask a doctor if rash occurs. When using this product, keep out of eyes. Rinse with water to remove. Keep out of reach of children. If swallowed, get medical help or contact a poison control center right away.

Directions:

- Apply liberally 15 minutes before sun exposure.
- Use a water resistant product if swimming or sweating.
- Reapply:
  - At least every 2 hours
- Children under 6 months: Ask a doctor
- Sun Protection Measures:Spending time in the sun increases your risk of skin cancer and early skin aging. To decrease this risk, regularly use a sunscreen with a Broad Spectrum SPF value of 15 or higher and other sun protection measures including:
  - Limit time in the sun, especially from 10 a.m. - 2 p.m.
  - Wear long-sleeved shirts, pants, hats, and sunglasses

Inactive Ingredients:

Capric/Caprylic Triglyceride, Ceramide 3, Cyclohexasiloxane, Cyclopentasiloxane, Dimethicone, Dimethicone Crosspolymer, Dimethicone/Vinyl Dimethicone Crosspolymer, Dimethiconol, Hydrogen Dimethicone, PEG-10 Dimethicone, Polyhydroxystearic Acid, Tetrahexyldecyl Ascorbate, Tocopheryl Acetate, Vinyl Dimethicone/Hydrogen Dimethicone Silsesquioxane Crosspolymer

Other Information:

- Protect this product from excessive heat and direct sun.

Keep out of reach of children.

Principal Display Panel – Carton Label

AM
REPLENISH

Non-Tinted
SPF 40

TIZO®

PHOTOCEUTICAL®

Enhances, protects &
neutralizes free radicals

Mineral Sunscreen

Ceramides

Antioxidants C & E

featuring

SKIN FIRM TECHNOLOGY®

Broad Spectrum SPF 40

Net Wt. 1.75 oz/50 g

Principal Display Panel – Tube Label

TIZO®

PHOTOCEUTICAL

AM
REPLENISH

Non-Tinted

Mineral Sunscreen

Ceramides

Antioxidants C & E

featuring

SKIN FIRM TECHNOLOGY®

SPF 40
Broad Spectrum

1.75 Fl. Oz/50 mL